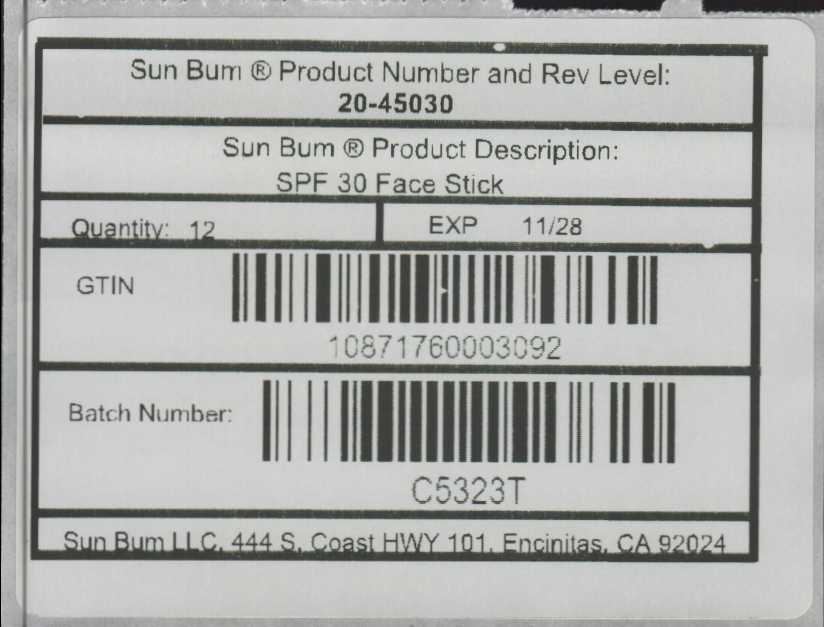 DRUG LABEL: SPF 30 Sunscreen Stick
NDC: 63645-329 | Form: STICK
Manufacturer: OraLabs
Category: otc | Type: HUMAN OTC DRUG LABEL
Date: 20251222

ACTIVE INGREDIENTS: AVOBENZONE 30 mg/1 g; HOMOSALATE 100 mg/1 g; OCTISALATE 50 mg/1 g; OCTOCRYLENE 100 mg/1 g
INACTIVE INGREDIENTS: PARAFFIN 240 mg/1 g; ETHYLHEXYL PALMITATE 200 mg/1 g

Drug Facts

Active ingredient

Avobenzone 3.0%, Homosalate 10.0%, Octisalate 5.0%, Octocrylene 10%................Sunscreen

Purpose

Sunscreen

Keep Out of Reach of Children

If swallowed get medical help or contact a Poison Control Center immediately.

Uses

Helps prevent sunburn. If used as directed with other sun protection measures (see Directions). Decreases the risk of skin cancer and early skin aging caused by the sun.

Warnings

For external use only: Do not use on damaged or broken skin. When using this product keep out of eyes. Rinse with water to remove. Stop use and ask a doctor: if rash or irritation develops and lasts.

Directions

Apply liberally 15 minutes before sun exposure • reapply: after 80 minutes

of swimming or sweating • immediately after towel drying • at least every 2 hours • Sun

Protection Measures.Spending time in the sun increases your risk of skin cancer and

early skin aging • To decrease the risk, regularly use a sunscreen with a broad spectrum

SPF of 15 or higher and other sun protection measures including: limit time in the sun,

especially from 10 a.m. -2 p.m. • wear long-sleeve shirts, pants, hats and sunglasses.

Inactive Ingredients

Paraffin wax, octyl palmitate, ozokerite, euphorbia cerifera (candelilla) wax, beeswax, butyloctyl salicylate, fragrance, polyethylene, polycrylene, cetyl alcohol, tocopheryl acetate, ascorbyl palmitate